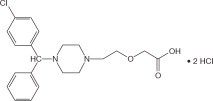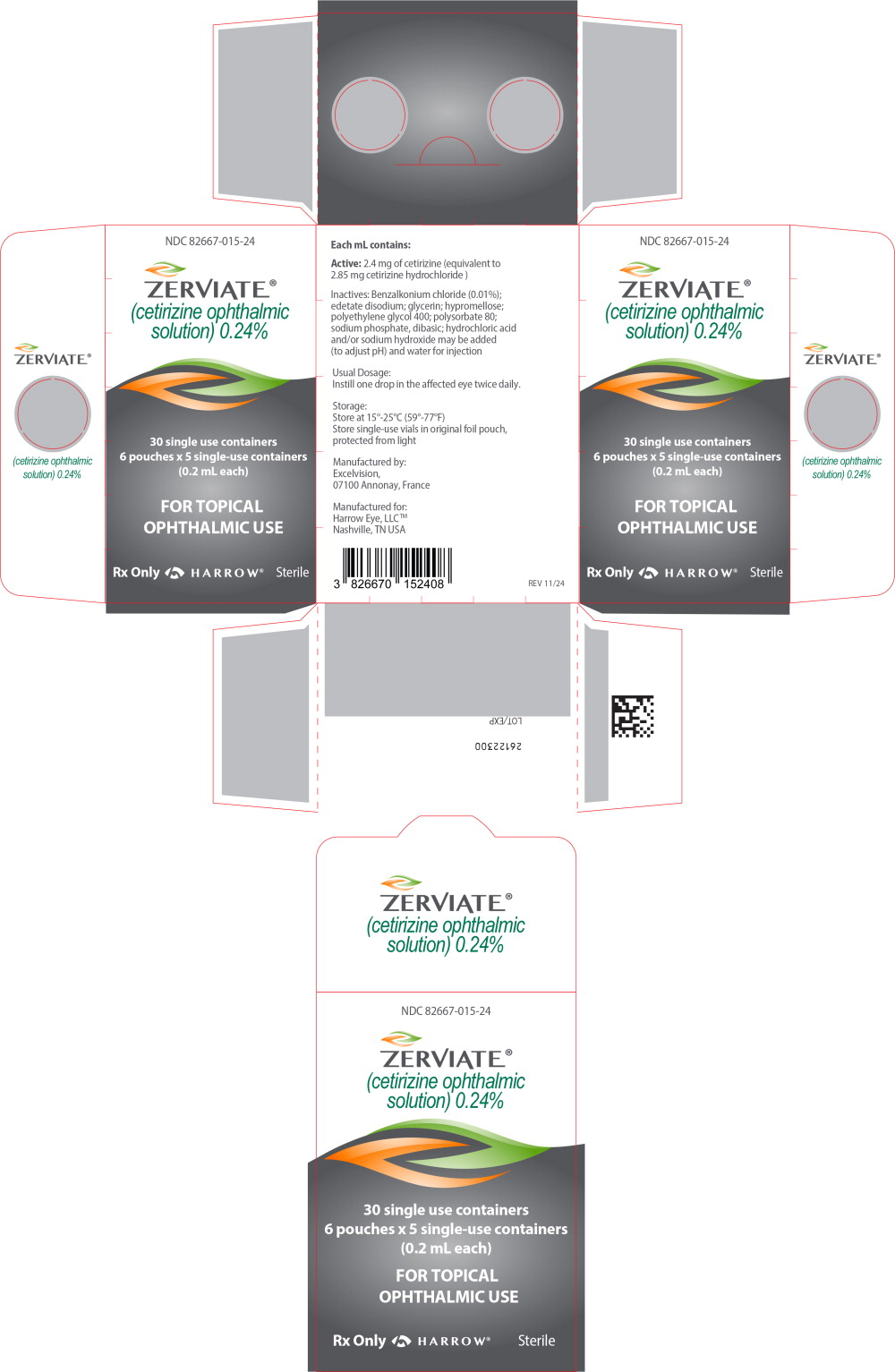 DRUG LABEL: ZERVIATE
NDC: 82667-015 | Form: FOR SOLUTION
Manufacturer: Harrow Eye, LLC
Category: prescription | Type: HUMAN PRESCRIPTION DRUG LABEL
Date: 20250423

ACTIVE INGREDIENTS: CETIRIZINE 2.4 mg/1 mL
INACTIVE INGREDIENTS: BENZALKONIUM CHLORIDE; EDETATE DISODIUM; GLYCERIN; HYPROMELLOSE 2910 (4000 MPA.S); POLYETHYLENE GLYCOL 400; POLYSORBATE 80; SODIUM PHOSPHATE, DIBASIC; HYDROCHLORIC ACID; SODIUM HYDROXIDE; WATER

HIGHLIGHTS OF PRESCRIBING INFORMATION

These highlights do not include all the information needed to use ZERVIATE®safely and effectively. See full prescribing information for ZERVIATE®.
ZERVIATE®(cetirizine ophthalmic solution) 0.24%, for topical ophthalmic use
Initial U.S. Approval: 1995

RECENT MAJOR CHANGES

Dosage and Administration (2) | 2/2020
Warnings and Precautions (5.1) | 2/2020

1 INDICATIONS AND USAGE

ZERVIATE®(cetirizine ophthalmic solution) 0.24% is a histamine-1 (H1) receptor antagonist indicated for treatment of ocular itching associated with allergic conjunctivitis. (1)

2 DOSAGE AND ADMINISTRATION

The recommended dose is one drop in each affected eye twice daily. (2)

3 DOSAGE FORMS AND STRENGTHS

Ophthalmic solution: 2.4 mg cetirizine in 1 mL sterile solution (0.24%). (3)

4 CONTRAINDICATIONS

None. (4)

5 WARNINGS AND PRECAUTIONS

Contamination of Tip and Solution. To prevent contaminating the dropper tip and solution, advise patients not to touch the eyelids or surrounding areas with the dropper tip of the bottle or tip of the single-use container. (5.1)

6 ADVERSE REACTIONS

The most common adverse reactions (1–7%) were ocular hyperemia, instillation site pain, and visual acuity reduced. (6)

To report SUSPECTED ADVERSE REACTIONS, contact Harrow at 1-833-4HARROW(427769) or FDA at 1-800-FDA-1088 orwww.fda.gov/medwatch.

FULL PRESCRIBING INFORMATION

1 INDICATIONS AND USAGE

ZERVIATE®(cetirizine ophthalmic solution) 0.24% is indicated for the treatment of ocular itching associated with allergic conjunctivitis.

2 DOSAGE AND ADMINISTRATION

The recommended dosage of ZERVIATE® is to instill one drop in each affected eye twice daily (approximately 8 hours apart).

The single-use containers are to be used immediately after opening and can be used to dose both eyes. Discard the single-use container and any remaining contents after administration. The single-use containers should be stored in the original foil pouch until ready to use.

3 DOSAGE FORMS AND STRENGTHS

Cetirizine ophthalmic solution, 0.24% is a sterile, buffered, clear, colorless aqueous solution containing cetirizine 0.24% (equivalent to cetirizine hydrochloride 0.29%).

4 CONTRAINDICATIONS

None.

5 WARNINGS AND PRECAUTIONS

5.1 Contamination of Tip and Solution

As with any eye drop, care should be taken not to touch the eyelids or surrounding areas with the dropper tip of the bottle or tip of the single-use container in order to avoid injury to the eye and to prevent contaminating the tip and solution. Keep the multi-dose bottle closed when not in use. Discard the single-use container after using in each eye.

5.2 Contact Lens Wear

Patients should be advised not to wear a contact lens if their eye is red.

ZERVIATE®should not be instilled while wearing contact lenses. Remove contact lenses prior to instillation of ZERVIATE®. The preservative in ZERVIATE®, benzalkonium chloride, may be absorbed by soft contact lenses. Lenses may be reinserted 10 minutes following administration of ZERVIATE®.

6 ADVERSE REACTIONS

Because clinical trials are conducted under widely varying conditions, adverse reaction rates observed in the clinical trial of a drug cannot be directly compared to rates in clinical trials of another drug and may not reflect the rates in practice.

In seven clinical trials, patients with allergic conjunctivitis or those at a risk of developing allergic conjunctivitis received one drop of either cetirizine (N=511) or vehicle (N=329) in one or both eyes. The most commonly reported adverse reactions occurred in approximately 1–7% of patients treated with either ZERVIATE®or vehicle. These reactions were ocular hyperemia, instillation site pain, and visual acuity reduced.

8 USE IN SPECIFIC POPULATIONS

8.1 Pregnancy

Risk Summary

There were no adequate or well-controlled studies with ZERVIATE®in pregnant women.

Cetirizine should be used in pregnancy only if the potential benefit justifies the potential risk to the fetus.

Data

Animal Data

Cetirizine was not teratogenic in mice, rats, or rabbits at oral doses up to 96, 225, and 135 mg/kg, respectively (approximately 1300, 4930, and 7400 times the maximum recommended human ophthalmic dose (MRHOD), on a mg/m^2basis).

8.2 Lactation

Risk Summary

Cetirizine has been reported to be excreted in human breast milk following oral administration. Multiple doses of oral dose cetirizine (10 mg tablets once daily for 10 days) resulted in systemic levels (Mean Cmax= 311 ng/mL) that were 100 times higher than the observed human exposure (Mean Cmax= 3.1 ng/ mL) following twice daily administration of cetirizine ophthalmic solution 0.24% to both eyes for one week [see Clinical Pharmacology (12.3)] . Comparable bioavailability has been found between the tablet and syrup dosage forms. However, it is not known whether the systemic absorption resulting from topical ocular administration of ZERVIATE®could produce detectable quantities in human breast milk.

There is no adequate information regarding the effects of cetirizine on breastfed infants, or the effects on milk production to inform risk of ZERVIATE®to an infant during lactation. The developmental and health benefits of breastfeeding should be considered along with the mother's clinical need for ZERVIATE®and any potential adverse effects on the breastfed child from ZERVIATE®.

8.4 Pediatric Use

The safety and effectiveness of ZERVIATE®(cetirizine ophthalmic solution) 0.24% has been established in pediatric patients two years of age and older. Use of ZERVIATE®in these pediatric patients is supported by evidence from adequate and well-controlled studies of ZERVIATE®in pediatric and adult patients.

8.5 Geriatric Use

No overall differences in safety or effectiveness have been observed between elderly and younger patients.

11 DESCRIPTION

ZERVIATE®is a sterile ophthalmic solution containing cetirizine, which is a histamine-1 (H1) receptor antagonist, for topical administration to the eyes. Cetirizine hydrochloride is a white, crystalline, water-soluble powder with a molecular weight of 461.8 and a molecular formula of C21H25ClN2O3•2HCl. The chemical structure is presented below:

Chemical Name:

(RS)-2-[2-[4-[(4-Chlorophenyl) phenylmethyl] piperazin-1-yl] ethoxy] acetic acid, dihydrochloride

Each mL of ZERVIATE®contains an active ingredient [cetirizine 2.40 mg (equivalent to 2.85 mg of cetirizine hydrochloride)] and the following inactive ingredients: benzalkonium chloride 0.010% (preservative); glycerin; sodium phosphate, dibasic; edetate disodium; polyethylene glycol 400; polysorbate 80; hypromellose; hydrochloric acid/sodiumhydroxide (to adjust pH); and water for injection. ZERVIATE®solution has a pH of approximately 7.0 and osmolality of approximately 300 mOsm/kg.

12 CLINICAL PHARMACOLOGY

12.1 Mechanism of Action

ZERVIATE®, an antihistamine, is a histamine-1 (H1) receptor antagonist. Its effects are mediated via selective inhibition of H1 histamine receptors. The antihistaminic activity of cetirizine has been documented in a variety of animal and human models. In vivoand ex vivoanimal models have shown negligible anticholinergic and antiserotonergic activity. In vitroreceptor binding studies have shown no measurable affinity for other than H1 receptors.

12.3 Pharmacokinetics

In healthy subjects, bilateral topical ocular dosing of one drop of ZERVIATE®resulted in a mean cetirizine plasma Cmaxof 1.7 ng/mL following a single dose and 3.1 ng/mL after twice-daily dosing for one week. The observed mean terminal half-life of cetirizine was 8.6 hours following a single dose and 8.2 hours after twice-daily dosing of ZERVIATE®for one week.

13 NONCLINICAL TOXICOLOGY

13.1 Carcinogenesis, Mutagenesis, Impairment of Fertility

Carcinogenicity

In a 2-year carcinogenicity study in rats, orally administered cetirizine was not carcinogenic at dietary doses up to 20 mg/ kg (approximately 550 times the MRHOD, on a mg/m^2basis). In a 2-year carcinogenicity study in mice, cetirizine caused an increased incidence of benign liver tumors in males at a dietary dose of 16 mg/kg (approximately 220 times the MRHOD, on a mg/m^2basis). No increase in the incidence of liver tumors was observed in mice at a dietary dose of 4 mg/kg (approximately 55 times the MRHOD, on a mg/m^2basis). The clinical significance of these findings during long-term use of cetirizine is not known.

Mutagenesis

Cetirizine was not mutagenic in the Ames test or in an in vivomicronucleus test in rats.

Cetirizine was not clastogenic in the human lymphocyte assay or the mouse lymphoma assay.

Impairment of Fertility

In a fertility and general reproductive performance study in mice, cetirizine did not impair fertility at an oral dose of 64 mg/kg (approximately 875 times the MRHOD on a mg/m^2basis).

14 CLINICAL STUDIES

The efficacy of ZERVIATE®(cetirizine ophthalmic solution) 0.24% was established in three randomized, double-masked, placebocontrolled, conjunctival allergen challenge (CAC) clinical trials in patients with a history of allergic conjunctivitis. Onset and duration of action were evaluated in two of these trials in which patients were randomized to receive ZERVIATE®or vehicle ophthalmic solutions. Patients were evaluated with an ocular itching severity score ranging from 0 (no itching) to 4 (incapacitating itch) at several time points after CAC administration. Table 1displays data from the mean ocular itching severity scores after ocular administration of an antigen using the CAC model. A one unit difference compared to vehicle is considered a clinically meaningful change in the ocular itching severity score.

Patients treated with ZERVIATE®demonstrated statistically and clinically significantly less ocular itching compared to vehicle at 15 minutes and 8 hours after treatment.

Table 1 Itching Scores in the ITT Population by Treatment Group and Treatment Difference
 | Study 1 |  |  |  | Study 2
Statistics | 15 minutes post-treatment |  | 8 hours post-treatment |  | 15 minutes post-treatment |  | 8 hours post-treatment
Statistics | ZERVIATE N=50 | Vehicle N=50 | ZERVIATE N=50 | Vehicle N=50 | ZERVIATE N=51 | Vehicle N=50 | ZERVIATE N=51 | Vehicle N=50
3 Minute Post-CAC
Mean | 1.00 | 2.38 | 1.76 | 2.69 | 1.01 | 2.54 | 1.94 | 2.86
Treatment Difference (95% CI)^1 | -1.38 (-1.72, -1.05)* |  | -0.93 (-1.26, -0.61)* |  | -1.53 (-1.92, -1.15)* |  | -0.92 (-1.25, -0.58)*
5 Minute Post-CAC
Mean | 1.18 | 2.43 | 1.85 | 2.74 | 1.17 | 2.51 | 2.03 | 2.94
Treatment Difference (95% CI)^1 | -1.25 (-1.58, -0.91)* |  | -0.89 (-1.24, -0.54)* |  | -1.34 (-1.71, -0.97)* |  | -0.90 (-1.23, -0.57)*
7 Minute Post-CAC
Mean | 1.11 | 2.11 | 1.54 | 2.53 | 1.15 | 2.23 | 1.82 | 2.66
Treatment Difference (95% CI)^1 | -1.00 (-1.35, -0.65)* |  | -0.99 (-1.40, -0.59)* |  | -1.07 (-1.46, -0.69)* |  | -0.84 (-1.21, -0.48)*
^1Treatment difference values shown are the group mean active minus the group mean vehicle at each post-CAC time point.
* p<0.05

16 HOW SUPPLIED/STORAGE AND HANDLING

ZERVIATE®is a sterile, buffered, clear, colorless aqueous solution containing cetirizine 0.24% (equivalent to cetirizine hydrochloride 0.29%) supplied in a white low-density polyethylene multi-dose ophthalmic bottle with a low-density polyethylene dropper tip and a white polypropylene cap. ZERVIATE®is supplied in a 7.5 mL bottle that contains 5 mL and a 10 mL bottle that contains 7.5 mL cetirizine ophthalmic solution, 2.40 mg [equivalent to 2.85 mg cetirizine hydrochloride in one mL solution]. ZERVIATE®is also supplied in 5 low-density polyethylene 0.2 mL single-use containers within a foil pouch.

Carton of 30 single-use containers NDC 82667-015-24

STORAGE AND HANDLING

Storage:Store at 15°C to 25°C (59°F to 77°F).

Single-use containers should be stored in the original foil pouch.

17 PATIENT COUNSELING INFORMATION

- Risk of Contamination: Advise patients not to touch dropper tip to eyelids or surrounding areas, as this may contaminate the dropper tip and ophthalmic solution. Advise patients to keep the bottle closed when not in use. Advise patients to discard single-use containers after each use.
- Concomitant Use of Contact Lenses: Advise patients not to wear contact lenses if their eyes are red. Advise patients that ZERVIATE®should not be used to treat contact lens-related irritation. Advise patients to remove contact lenses prior to instillation of ZERVIATE®. The preserative in ZERVIATE®solution, benzalkonium chloride, may be absorbed by soft contact lenses. Lenses may be reinserted 10 minutes following administration of ZERVIATE®.
- Administration: Advise patients that the solution from one single-use container is to be used immediately after opening. Advise patients that the single-use container can be used to dose both eyes. Discard the single-use container and remaining contents immediately after administration.
- Storage of Single-use Containers: Instruct patients to store single-use containers in the original foil pouch until ready to use.

Rev 11/2024

Manufactured for:
Harrow Eye, LLCTM
Nashville, TN USA

U.S. Patents: 8,829,005; 9,254,286; 9,750,684; 9,993,471

Principal Display Panel – 2.5 mL Carton Label

NDC 82667-015-24

ZERVIATE®

(cetirizine ophthalmic
solution) 0.24%

30 single use containers

6 pouches x 5 single-use containers
(0.2 mL each)

FOR TOPICAL
OPHTHALMIC USE

Rx Only HARROW® Sterile